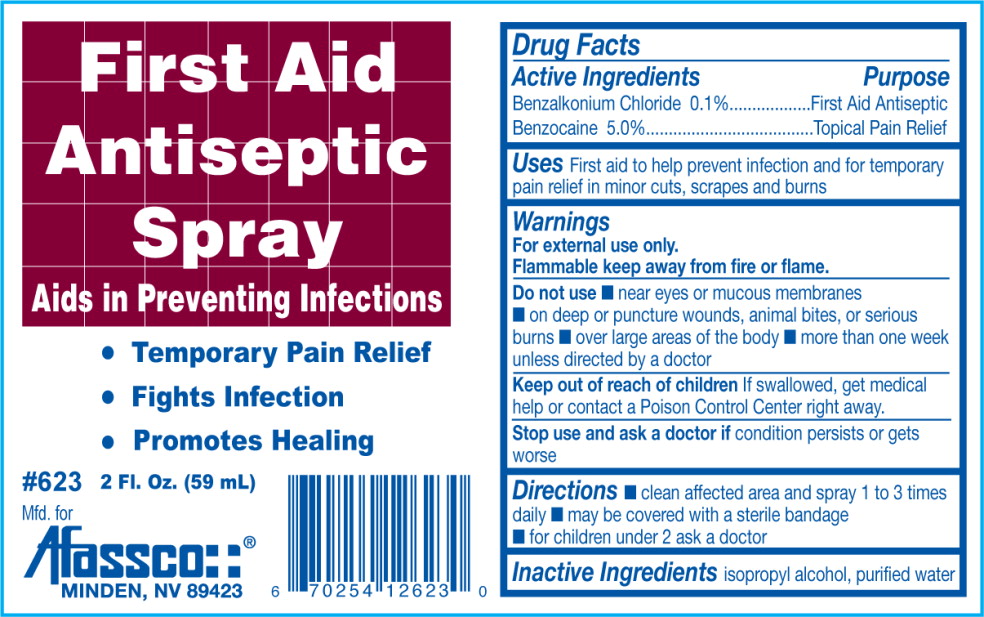 DRUG LABEL: Antiseptic
NDC: 51532-5300 | Form: SPRAY
Manufacturer: Afassco Inc.
Category: otc | Type: HUMAN OTC DRUG LABEL
Date: 20230112

ACTIVE INGREDIENTS: benzalkonium chloride 1 mg/1 mL; benzocaine 50 mg/1 mL
INACTIVE INGREDIENTS: isopropyl alcohol; water

Drug Facts

Active Ingredients

Benzalkonium Chloride 0.1%

Benzocaine 5.0%

Purpose

First Aid Antiseptic

Topical Pain Relief

Uses

First aid to help prevent infection and for temporary pain relief in minor cuts, scrapes and burns

Warnings

For external use only.
Flammable keep away from fire or flame.

Do not use

- near eyes or mucous membranes
- on deep or puncture wounds, animal bites, or serious burns
- over large areas of the body
- more than one week unless directed by a doctor

Keep out of reach of children If swallowed, get medical help or contact a Poison Control Center right away.

Stop use and ask doctor if condition persists or gets worse

Directions

- clean affected area and spray 1 to 3 times daily
- may be covered with a sterile bandage
- children under 2 ask a doctor.

Inactive ingredients

isopropyl alcohol, purified water

PRINCIPAL DISPLAY PANEL – bottle label

First Aid
Antiseptic
Spray

Aids in Preventing Infections

Temporary Pain Relief
Fights Infection
Promotes Healing

#623 2 Fl. Oz. (59 mL)

Mfd. For
Afassco
MINDEN, NV 89423

res